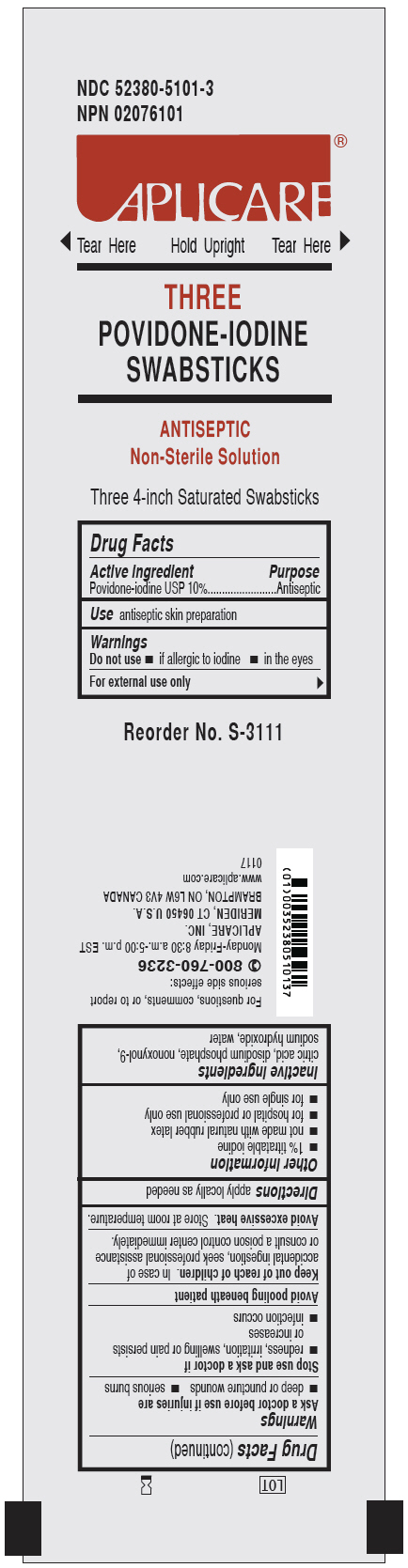 DRUG LABEL: Aplicare Povidone-iodine Triples
NDC: 52380-5101 | Form: SOLUTION
Manufacturer: Aplicare Products, LLC
Category: otc | Type: HUMAN OTC DRUG LABEL
Date: 20230802

ACTIVE INGREDIENTS: POVIDONE-IODINE 10 mg/1 mL
INACTIVE INGREDIENTS: SODIUM PHOSPHATE, DIBASIC; CITRIC ACID MONOHYDRATE; SODIUM HYDROXIDE; NONOXYNOL-9; WATER

5101 Aplicare Povidone-iodine Triples

Active ingredient

Povidone-iodine USP 10%

Purpose

Antiseptic

Use

antiseptic skin preparation

Warnings

- For external use only
- Avoid pooling beneath patient

Do not use

- • if allergic to iodine
- • in the eyes

Ask a doctor before use if injuries are

- • deep or puncture wounds
- • serious burns

Stop use and ask a doctor if

- • redness, irritation, swelling or pain persists or increases
- • infection occurs

Keep out of reach of children.

In case of accidental ingestion, seek professional assistance or consult a poison control center immediately.

Storage Information

Avoid excessive heat.Store at room temperature.

Directions

- apply locally as needed

Other information

- • 1% titratable iodine
- • not made with natural rubber latex
- • for hospital or professional use only
- • for single use only

Inactive ingredients

citric acid, disodium phosphate, nonoxynol-9, sodium hydroxide, water

Manufacturing Information

Manufactured by:

Aplicare Products, LLC

550 Research Parkway, Meriden, CT 06450 USA

Manufactured for:

Medline Industries, LP

Three Lakes Drive, Northfield, IL 60093 USA

Made in USA with domestic and foreign materials

1-800-633-5463

REF: APLS3111

0117